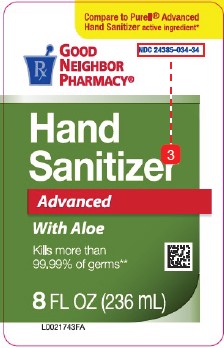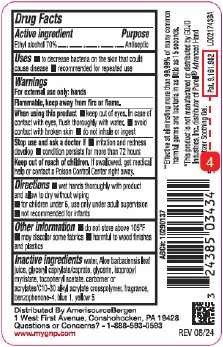 DRUG LABEL: Advanced Hand Sanitizer
NDC: 24385-034 | Form: GEL
Manufacturer: Amerisource Bergen
Category: otc | Type: HUMAN OTC DRUG LABEL
Date: 20260129

ACTIVE INGREDIENTS: ALCOHOL 700 mg/1 mL
INACTIVE INGREDIENTS: WATER; ALOE VERA LEAF; GLYCERYL CAPRYLATE/CAPRATE; GLYCERIN; ISOPROPYL MYRISTATE; .ALPHA.-TOCOPHEROL ACETATE; CARBOMER COPOLYMER TYPE B (ALLYL PENTAERYTHRITOL CROSSLINKED); SULISOBENZONE; FD&C BLUE NO. 1; FD&C YELLOW NO. 5

Good Neighbor Pharmacy 439.001/439AC rev 1
Advanced Hand Sanitizer with Aloe

Active ingredient

Ethyl Alcohol 70%

Purpose

Antiseptic

Uses

- to decrease bacteria on the skin that could cause disease
- recommended for repeated use

Warnings

For external use only: hands

Flammable, keep away from fire or flame.

When using this product

- keep out of eyes. In case of contact with eyes, flush thoroughly with water.
- avoid contact with broken skin
- do not inhale or ingest

Stop use and ask a doctor if

- irritation and redness develop
- condition persists for more than 72 hours

Keep out of reach of children.

If swallowed, get medical help or contact a Poison Control Center right away.

Directions

- wet hands thoroughly with product and allow to dry without wiping
- for children under 6, use only under adult supervision
- not recommended for infants

Other information

- do not store above 105⁰ F
- may discolor some fabrics
- harmful to wood finishes and plastics

Inactive ingredients

water, Aloe barbadensis leaf juice, glyceryl caprylate/caprate, glycerin, isopropyl myristate, tocopheryl acetate, carbomer or acrylates/C10-30 alkyl acrylate crosspolymer, fragrance, benzophenone-4, blue 1, yellow 5

ADVERSE REACTION

DISTRIBUTED BY AmerisourceBergen

1 West First Avenue, Conshohocken, PA 19428

Questions or Concerns? - 1-888-593-0593

www.mygnp.com

Claim

**Effective at eliminating more than 99.99% of many common harmful germs and bacteria in as little as 15 seconds.

Disclaimer

*This product is not manufactured or distributed by GOJO Industries, Inc. distributor of Purell®Advanced Hand Sanitizer Soothing Gel.

Principal Display Panel

Compare to Purell®Advanced Hand Sanitizer active ingredient*

Good Neighbor Pharmacy®

NDC 24385-034-34

Hand Sanitizer

Advanced

With Aloe

Kills more than 99.99% of germs*

8 FL OZ (236 mL)